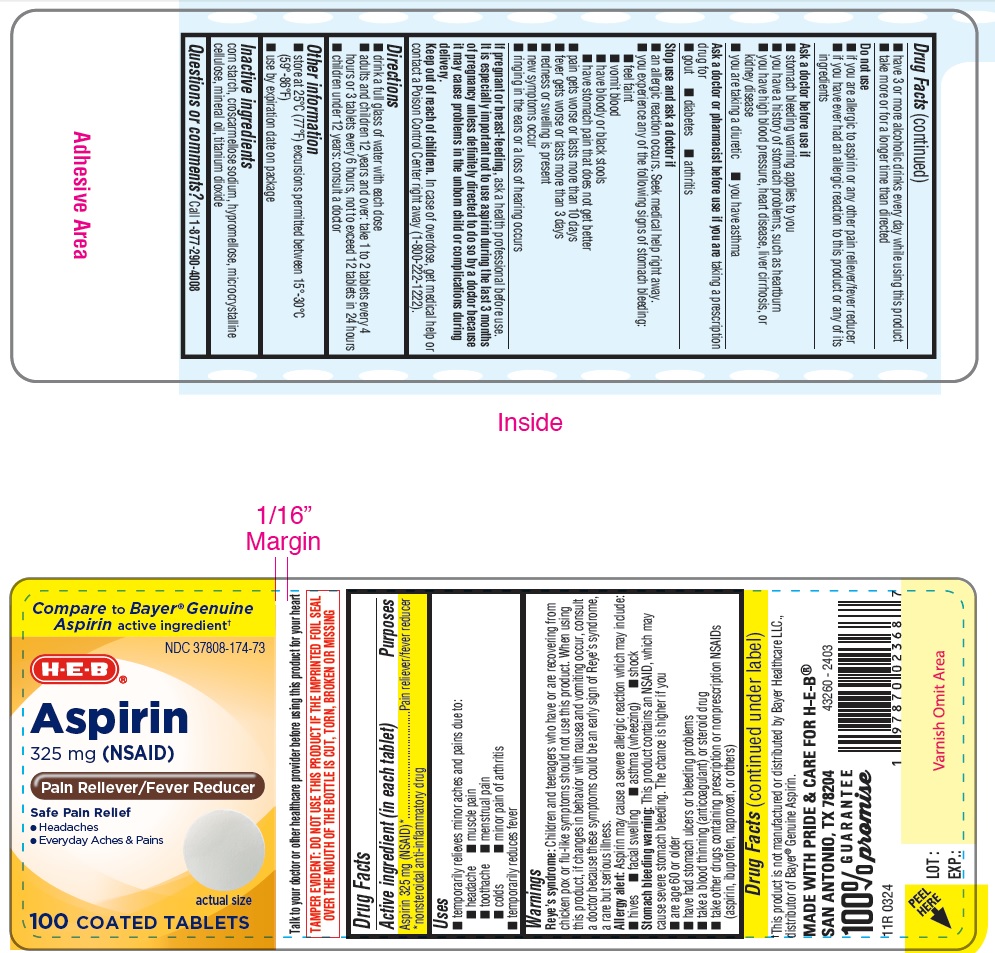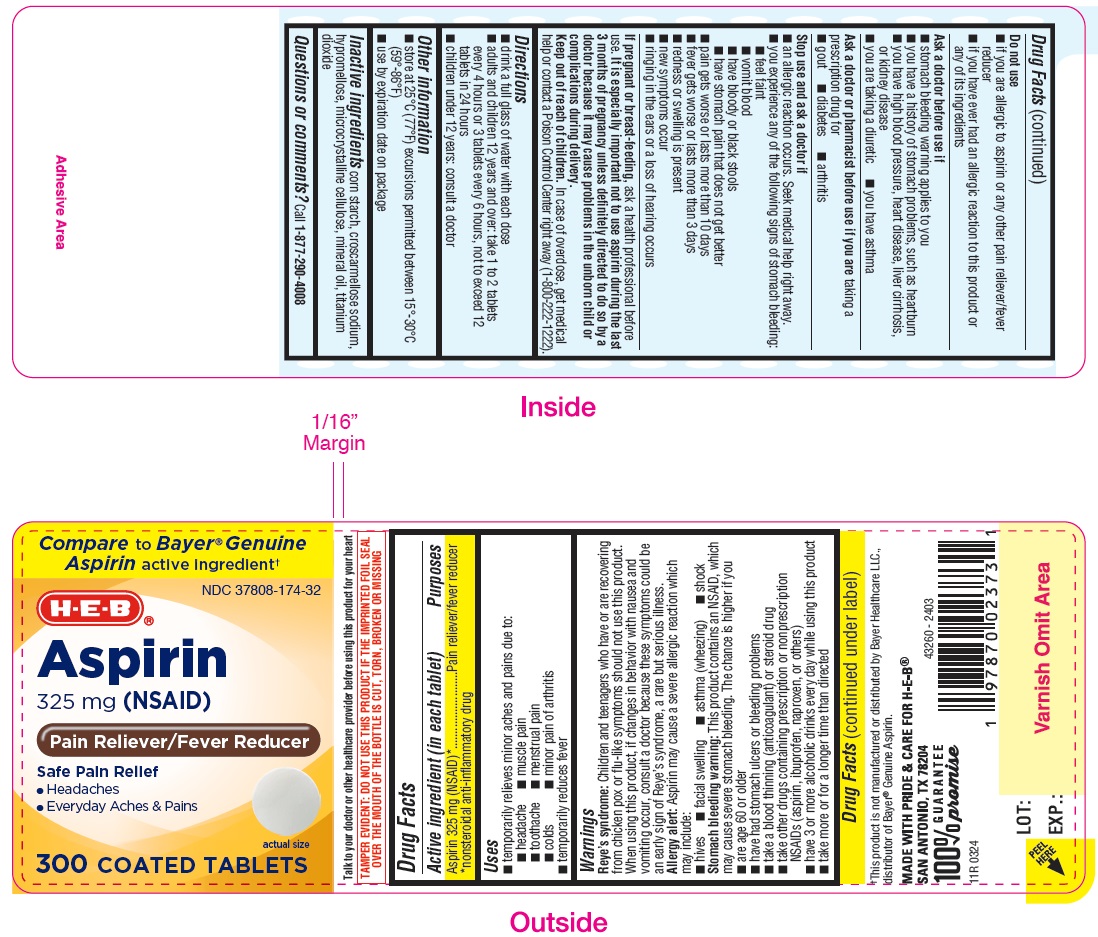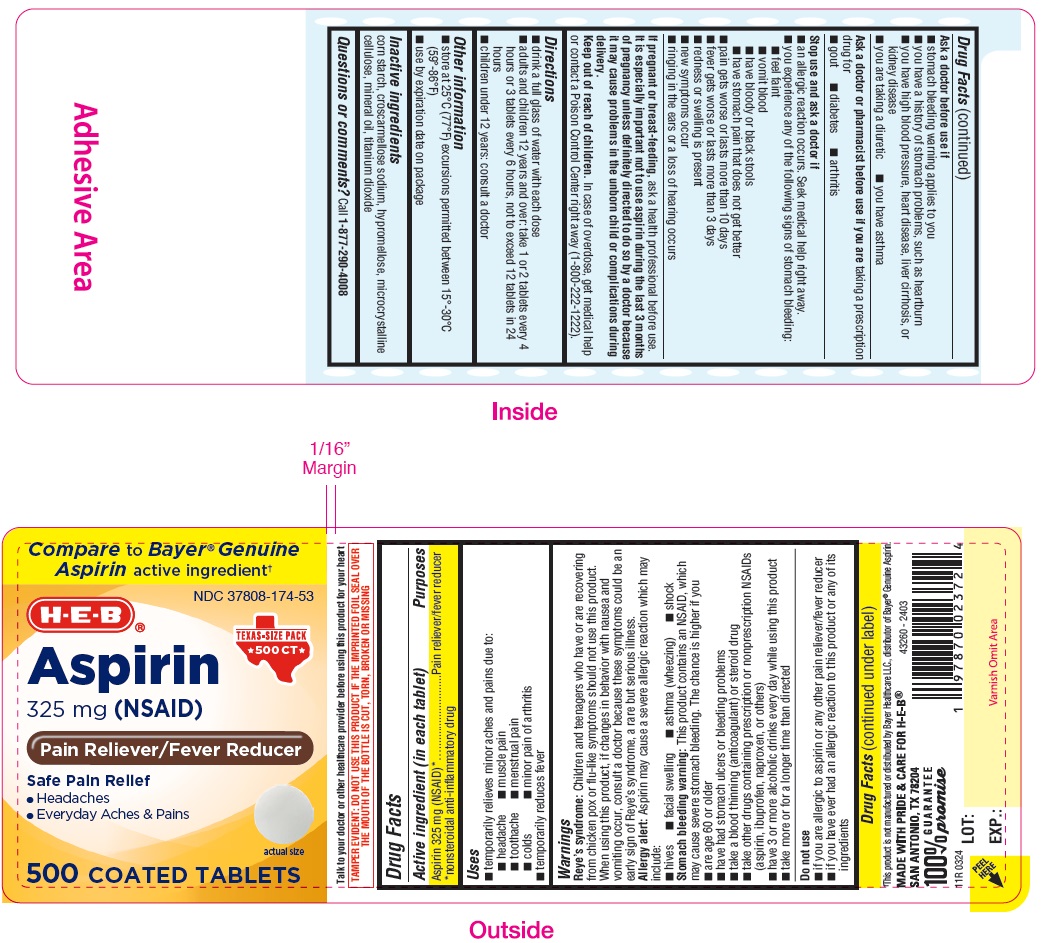 DRUG LABEL: ASPIRIN
NDC: 37808-174 | Form: TABLET, COATED
Manufacturer: H-E-B
Category: otc | Type: HUMAN OTC DRUG LABEL
Date: 20240607

ACTIVE INGREDIENTS: ASPIRIN 325 mg/1 1
INACTIVE INGREDIENTS: CROSCARMELLOSE SODIUM; HYPROMELLOSES; CELLULOSE, MICROCRYSTALLINE; MINERAL OIL; TITANIUM DIOXIDE; STARCH, CORN

HEB Aspirin 325 mg tablets

Active ingredient (in each tablet)
Aspirin 325 mg (NSAID*)

*nonsteroidal anti-inflammatory drug

Purpose

Pain reliever

INDICATIONS AND USAGE

Uses

for the temporary relief of minor aches and pains due to

- headache
- colds
- menstrual pain
- muscle pain
- toothache
- minor pain of arthritis

or as directed by your doctor

Warnings

Reye's syndrome:Children and teenagers who have or are recovering from chicken pox or flu-like symptoms should not use this product. When using this product, if changes in behavior with nausea and vomiting occur, consult a doctor because these symptoms could be an early sign of Reye's syndrome, a rare but serious illness.

Allergy alert:Aspirin may cause a severe allergic reaction which may include:

- hives
- facial swelling
- shock
- asthma (wheezing)

Stomach bleeding warning:This product contains an NSAID, which may cause severe stomach bleeding. The chance is higher if you:

- are age 60 or older
- have had stomach ulcers or bleeding problems
- take a blood thinning (anticoagulant) or steroid drug
- have 3 or more alcoholic drinks every day while using this product
- take more or for a longer time than directed
- take other drugs containing prescription or nonprescription NSAIDs (aspirin, ibuprofen, naproxen, or others)

Do not use

- if you are allergic to aspirin or any other pain reliever/fever reducer

Ask a doctor before use if

- stomach bleeding warning applies to you
- you have a history of stomach problems, such as heartburn
- you have asthma
- you have high blood pressure, heart disease, liver cirrhosis, or kidney disease
- you are taking a diuretic
- you have not been drinking fluids
- you have lost a lot of fluid due to vomiting or diarrhea

Ask a doctor or pharmacist before use if you are

- taking a prescription drug for diabetes, gout, or arthritis
- taking any other drug
- under a doctor's care for any serious condition

Stop use and ask a doctor if

you experience any of the following signs of stomach bleeding:

- feel faint
- have bloody or black stools
- vomit blood
- have stomach pain that does not get better

pain gets worse or lasts more than 10 days

fever gets worse or lasts more than 3 days

redness or swelling is present in the painfull area

any new symptoms appear

ringing in the ears or a loss of hearing occurs

PREGNANCY OR BREAST FEEDING

If pregnant or breast-feeding,ask a health professional before use. It is especially important not to use aspirin during the last 3 months of pregnancy unless definitely directed to do so by a doctor because it may casue problems in the unborn child or complications during delivery.

Keep out of reach of children.In case of overdose, get medical help or contact a Poison Control Center right away.

Directions

drink a full glass of water with each dose

- adults and children 12 years and over: take 1 to 2 tablets every 4 hours while symptoms last. Do not take more than 12 tablets in 24 hours unless directed by a doctor
- children under 12 years: consult a doctor

Other information

- store at 25°C (77°F) excursions permitted between 15°-30°C (59°-86°F)
- use by expiration date on package

INACTIVE INGREDIENT

Inactive ingredientscorn starch, croscramellose sodium, hypromellose, microcrystalline cellulose, mineral oil, titanium dioxide